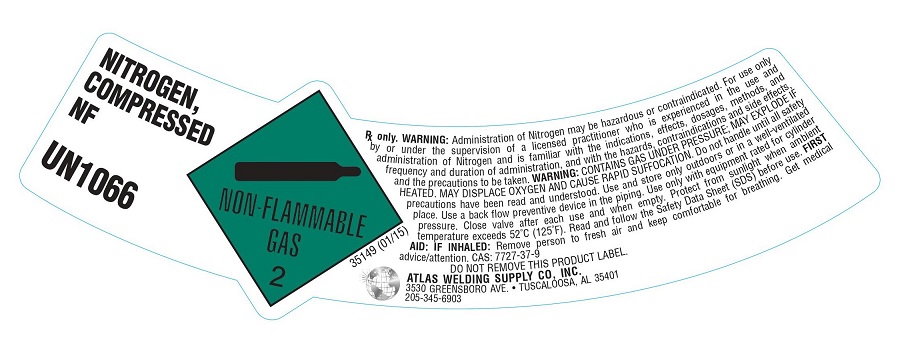 DRUG LABEL: Nitrogen
NDC: 51051-012 | Form: GAS
Manufacturer: Atlas Welding Supply Company, Inc.
Category: animal | Type: PRESCRIPTION ANIMAL DRUG LABEL
Date: 20251223

ACTIVE INGREDIENTS: NITROGEN 990 mL/1 L

Nitrogen

PACKAGE LABEL

NITROGEN, COMPRESSED NF UN1066
NON-FLAMMABLE GAS 2 NITROGEN NF
Rx only. WARNING: Administration of Nitrogen may be hazardous or contraindicated. For use only by or under the supervision of a licensed practitioner who is experienced in the use and administration of Nitrogen and is familiar with the indications, effects, dosages, methods, and frequency and duration of administration, and with the hazards, contraindications, and side effects and the precautions to be taken. WARNING: CONTAINS GAS UNDER PRESSURE; MAY EXPLODE IF HEATED. MAY DISPLACE OXYGEN AND CAUSE RAPID SUFFOCATION. Do not handle until all safety precautions have been read and understood. Use and store only outdoors or in a well-ventilated place. Use a back flow preventive device in the piping. Use only with equipment rated for cylinder pressure. Close valve after each use and when empty. Protect from sunlight when ambient temperature exceeds 52 degrees C (125 degrees F). Read and follow the Safety Data Sheet (SDS) before use. FIRST AID: IF INHALED: Remove person to fresh air and keep comfortable for breathing. Get medical advice/attention.
CAS: 7727-37-9 DO NOT REMOVE THIS PRODUCT LABEL.
ATLAS WELDING SUPPLY CO, INC. 3530 GREENSBORO AVE. . TUSCALOOSA, AL 35401 205-345-6903